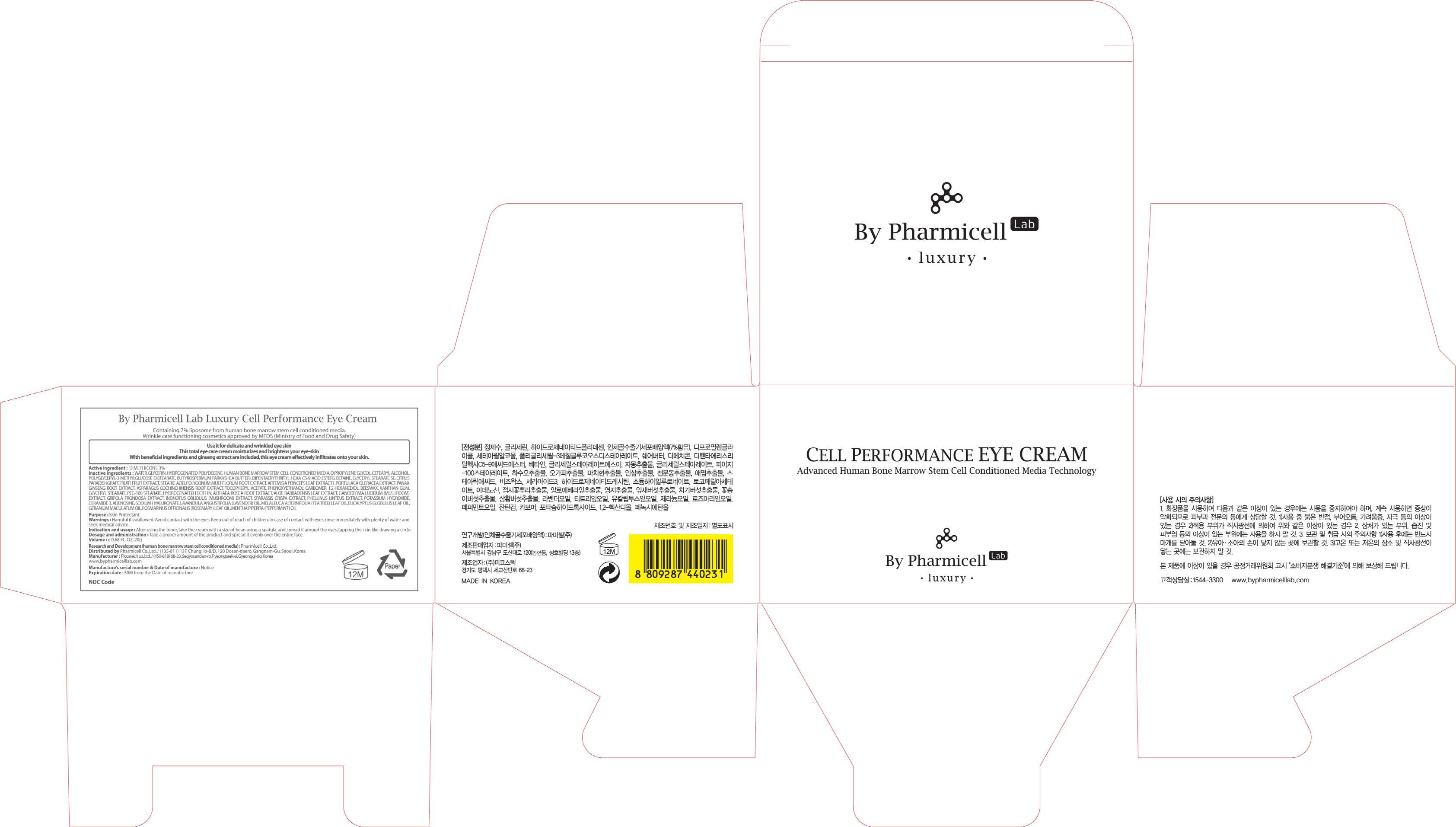 DRUG LABEL: Luxury Cell Performance Eye
NDC: 60949-150 | Form: CREAM
Manufacturer: Pharmicell Co., Ltd.
Category: otc | Type: HUMAN OTC DRUG LABEL
Date: 20140922

ACTIVE INGREDIENTS: DIMETHICONE 0.6 g/20 g
INACTIVE INGREDIENTS: WATER; GLYCERIN

ACTIVE INGREDIENT

Active ingredient : DIMETHICONE 3%

INACTIVE INGREDIENT

Inactive ingredients : WATER, GLYCERIN, HYDROGENATED POLYDECENE, HUMAN BONE MARROW STEM CELL CONDITIONED MEDIA, DIPROPYLENE GLYCOL, CETEARYL ALCOHOL, POLYGLYCERYL-3 METHYLGLUCOSE DISTEARATE, BUTYROSPERMUM PARKII(SHEA BUTTER), DIPENTAERYTHRITYL HEXA C5-9 ACID ESTERS, BETAINE, GLYCERYL STEARATE SE, CITRUS PARADISI (GRAPEFRUIT) FRUIT EXTRACT, STEARIC ACID, POLYGONUM MULTIFLORUM ROOT EXTRACT, ARTEMISIA PRINCEPS LEAF EXTRACT1, PORTULACA OLERACEA EXTRACT, PANAX GINSENG ROOT EXTRACT, ASPARAGUS COCHINCHINENSIS ROOT EXTRACT, TOCOPHERYL ACETATE, PHENOXYETHANOL, CARBOMER, 1,2-HEXANEDIOL, BEESWAX, XANTHAN GUM, GLYCERYL STEARATE, PEG-100 STEARATE, HYDROGENATED LECITHIN, ALTHAEA ROSEA ROOT EXTRACT, ALOE BARBADENSIS LEAF EXTRACT, GANODERMA LUCIDUM (MUSHROOM) EXTRACT, GRIFOLA FRONDOSA EXTRACT, INONOTUS OBLIQUUS (MUSHROOM) EXTRACT, SPARASSIS CRISPA EXTRACT, PHELLINUS LINTEUS EXTRACT, POTASSIUM HYDROXIDE, CERAMIDE 3, ADENOSINE, SODIUM HYALURONATE, LAVANDULA ANGUSTIFOLIA (LAVENDER) OIL, MELALEUCA ALTERNIFOLIA (TEA TREE) LEAF OIL, EUCALYPTUS GLOBULUS LEAF OIL, GERANIUM MACULATUM OIL, ROSMARINUS OFFICINALIS (ROSEMARY) LEAF OIL, MENTHA PIPERITA (PEPPERMINT) OIL

PURPOSE

Purpose : Skin Protectant

WARNINGS

Warnings : Harmful if swallowed. Avoid contact with the eyes. Keep out of reach of children. In case of contact with eyes, rinse immediately with plenty of water and seek medical advice.

KEEP OUT OF REACH OF CHILDREN

INDICATIONS & USAGE

Indication and usage : After using the toner, take the cream with a size of bean using a spatula, and spread it around the eyes, tapping the skin like drawing a circle.

DOSAGE & ADMINISTRATION

Dosage and administration : Take a proper amount of the product and spread it evenly over the entire face.